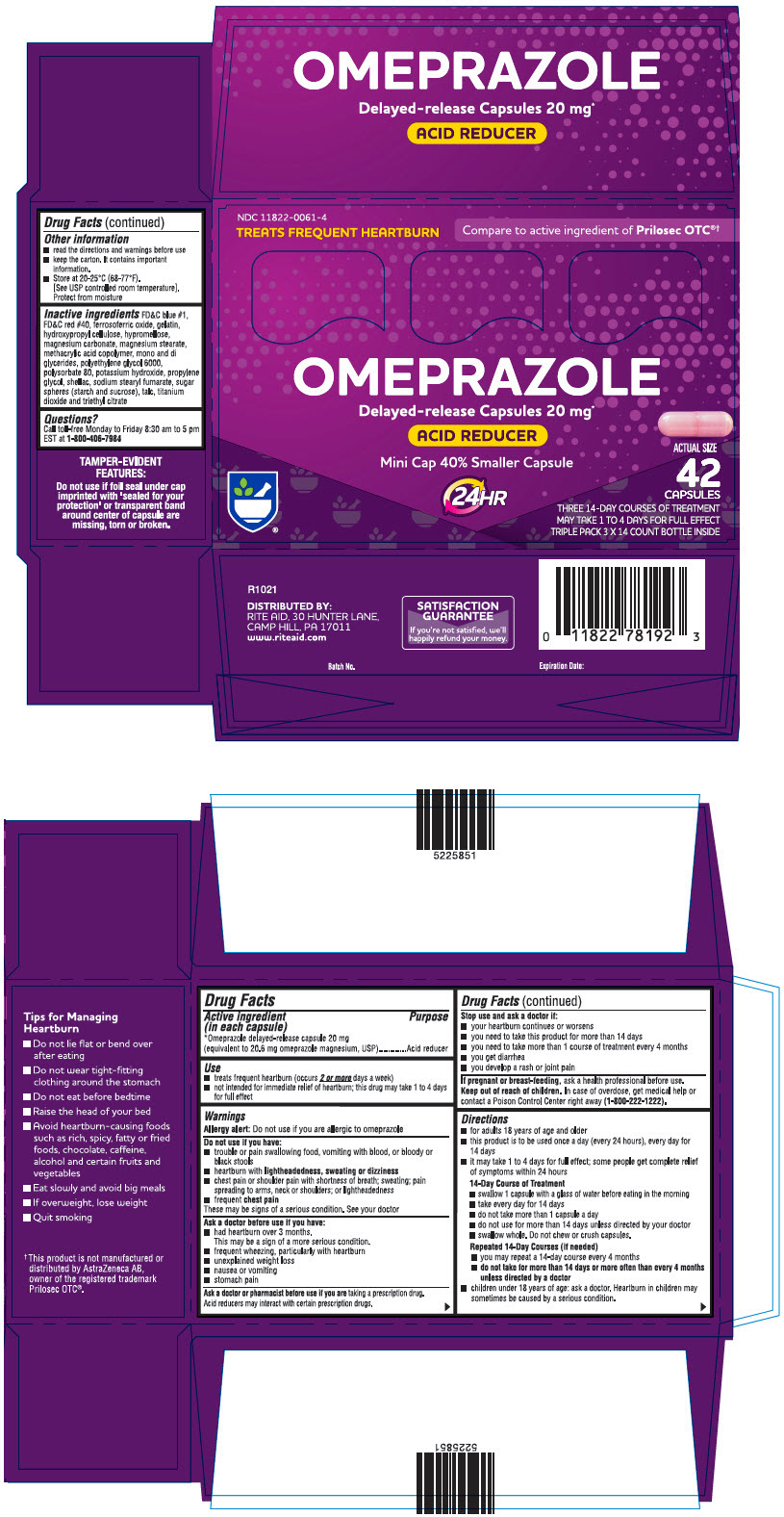 DRUG LABEL: omeprazole
NDC: 11822-0061 | Form: CAPSULE, DELAYED RELEASE
Manufacturer: Rite Aid
Category: otc | Type: HUMAN OTC DRUG LABEL
Date: 20220303

ACTIVE INGREDIENTS: OMEPRAZOLE MAGNESIUM 20.6 mg/1 1
INACTIVE INGREDIENTS: FERROSOFERRIC OXIDE; GELATIN, UNSPECIFIED; HYDROXYPROPYL CELLULOSE, UNSPECIFIED; HYPROMELLOSE 2208 (100 MPA.S); MAGNESIUM CARBONATE; MAGNESIUM STEARATE; METHACRYLIC ACID AND ETHYL ACRYLATE COPOLYMER; POLYSORBATE 80; POTASSIUM HYDROXIDE; PROPYLENE GLYCOL; SHELLAC; SODIUM STEARYL FUMARATE; TALC; TITANIUM DIOXIDE; TRIETHYL CITRATE; STARCH, CORN; SUCROSE; FD&C BLUE NO. 1; FD&C RED NO. 40; POLYETHYLENE GLYCOL 6000

Drug Facts

Active ingredient (in each capsule)

*Omeprazole delayed-release capsule 20 mg (equivalent to 20.6 mg omeprazole magnesium, USP)

Purpose

Acid reducer

Use

- treats frequent heartburn (occurs 2 or moredays a week)
- not intended for immediate relief of heartburn; this drug may take 1 to 4 days for full effect

Warnings

Allergy alert: Do not use if you are allergic to omeprazole

Do not use if you have:

■ trouble or pain swallowing food, vomiting with blood, or bloody or black stools

■ heartburn with lightheadedness, sweating or dizziness

■ chest pain or shoulder pain with shortness of breath; sweating; pain spreading to arms, neck or shoulders; or lightheadedness

■ frequent chest pain

These may be signs of a serious condition. See your doctor

Ask a doctor before use if you have:

■ had heartburn over 3 months. This may be a sign of a more serious condition.

■ frequent wheezing, particularly with heartburn

■ unexplained weight loss

■ nausea or vomiting

■ stomach pain

Ask a doctor or pharmacist before use if you are taking a prescription drug. Acid reducers may interact with certain prescription drugs.

Stop use and ask a doctor if:

■ your heartburn continues or worsens

■ you need to take this product for more than 14 days

■ you need to take more than 1 course of treatment every 4 months

■ you get diarrhea

■ you develop a rash or joint pain

If pregnant or breast-feeding, ask a health professional before use.

Keep out of reach of children. In case of overdose, get medical help or contact a Poison Control Center right away (1-800-222-1222).

Directions

- for adults 18 years of age and older

■ this product is to be used once a day (every 24 hours), every day for 14 days

■ it may take 1 to 4 days for full effect; some people get complete relief of symptoms within 24 hours

14-Day Course of Treatment

■ swallow 1 capsule with a glass of water before eating in the morning

■ take every day for 14 days

■ do not take more than 1 capsule a day

■ do not use for more than 14 days unless directed by your doctor

■ swallow whole. Do not chew or crush capsules.

Repeated 14-Day Courses (if needed)

■ you may repeat a 14-day course every 4 months

■ do not take for more than 14 days or more often than every 4 months unless directed by a doctor

■ children under 18 years of age: ask a doctor. Heartburn in children may sometimes be caused by a serious condition.

Other Safety Information

■ read the directions and warnings before use

■ keep the carton. It contains important information.

■ Store at 20-25°C (68-77°F). [See USP controlled room temperature]. Protect from moisture

Inactive Ingredients

FD&C blue #1, FD&C red #40, ferrosoferric oxide, gelatin, hydroxypropyl cellulose, hypromellose, magnesium carbonate, magnesium stearate, methacrylic acid copolymer, mono and diglycerides, polyethylene glycol 6000, polysorbate 80, potassium hydroxide, propylene glycol, shellac, sodium stearyl fumarate, sugar spheres (starch and sucrose), talc, titanium dioxide and triethyl citrate

Questions?

Call toll-free Monday to Friday 8:30 am to 5 pm EST at 1800-406-7984

PRINCIPAL DISPLAY PANEL - 42 Capsule Bottle Carton

NDC 11822-0061-4
TREATS FREQUENT HEARTBURN
Compare to the active ingredient of Prilosec OTC®†

OMEPRAZOLE
Delayed-release Capsules 20 mg*
ACID REDUCER
Mini Cap 40% Smaller Capsule

24 HR

ACTUAL SIZE

42
CAPSULES
THREE 14-DAY COURSES OF TREATMENT
MAY TAKE 1 TO 4 DAYS FOR FULL EFFECT
TRIPLE PACK 3 X 14 COUNT BOTTLE INSIDE